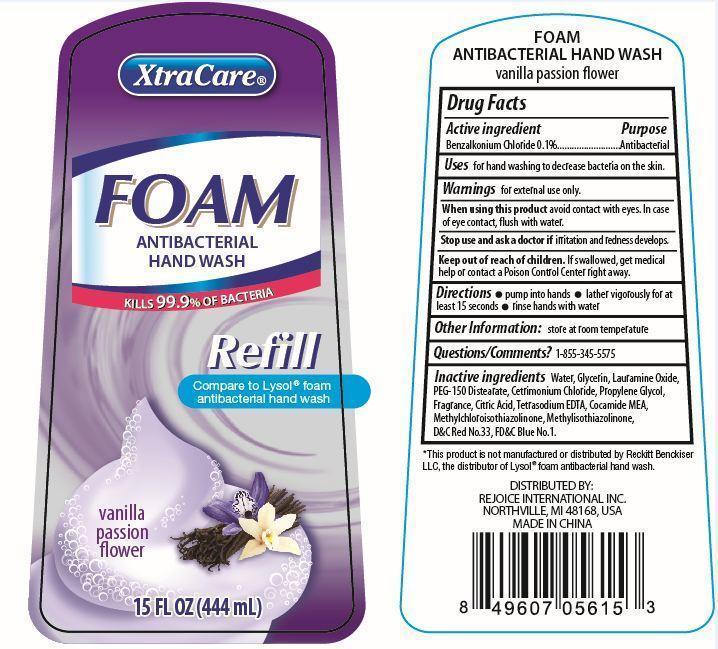 DRUG LABEL: XtraCare Foam Antibacterial Hand Wash
NDC: 57337-045 | Form: LIQUID
Manufacturer: Rejoice International
Category: otc | Type: HUMAN OTC DRUG LABEL
Date: 20240228

ACTIVE INGREDIENTS: BENZALKONIUM CHLORIDE 0.5 g/444 g
INACTIVE INGREDIENTS: WATER; GLYCERIN; LAURAMINE OXIDE; PEG-150 DISTEARATE; CETRIMONIUM CHLORIDE; PROPYLENE GLYCOL; CITRIC ACID MONOHYDRATE; EDETATE SODIUM; COCO MONOETHANOLAMIDE; METHYLCHLOROISOTHIAZOLINONE; METHYLISOTHIAZOLINONE; D&C RED NO. 33; FD&C BLUE NO. 1

XtraCare Foam Antibacterial Hand Wash

Active Ingredient Purpose

Benzalkonium Chloride 0.1% ............. Antibacterial

Uses

for hand washing to decrease bacteria on the skin

Keep out of reach of children. If swallowed, get medical help or contact a Poison Control Center right away.

INDICATIONS AND USAGE

XtraCare® Foam Antibacterial HAnd Wash

Kills 99.9% of bacteria

Refill

Compare to Lysol foam antibacterial hand wash

vanilla passion flower

15 Fl Oz (444mL)

Warnings

For external use only

When using this product avoid contact with eyes. In case of eye contact, flush with water.

Stop use and ask a doctor if irritation and redness develops.

Directions

- pump into hands
- lather vigorously for at least 15 seconds
- rinse hands with water

Inactive Ingredients

water, glycerin, lauramine oxide, PEG-150 distearate, cetrimonium chloride, propylene glycol, fragrance, citric acid, tetrasodium EDTA, cocamide MEA, methylchloroisothiazolinone, methylisothiazolinone, D&C red no.33, FD&C blue no.1

Other Information

store at room temperature

Questions/Comments? 1-855-345-5575

*this product is not manufactured or distributed by Reckitt Benckiser LLC, the distributor of Lysol® foam antibacterial hand wash.

DISTRIBUTED BY:

REJOICE INTERNATIONAL INC

NORTHVILLE, MI 48168, USA

MADE IN CHINA